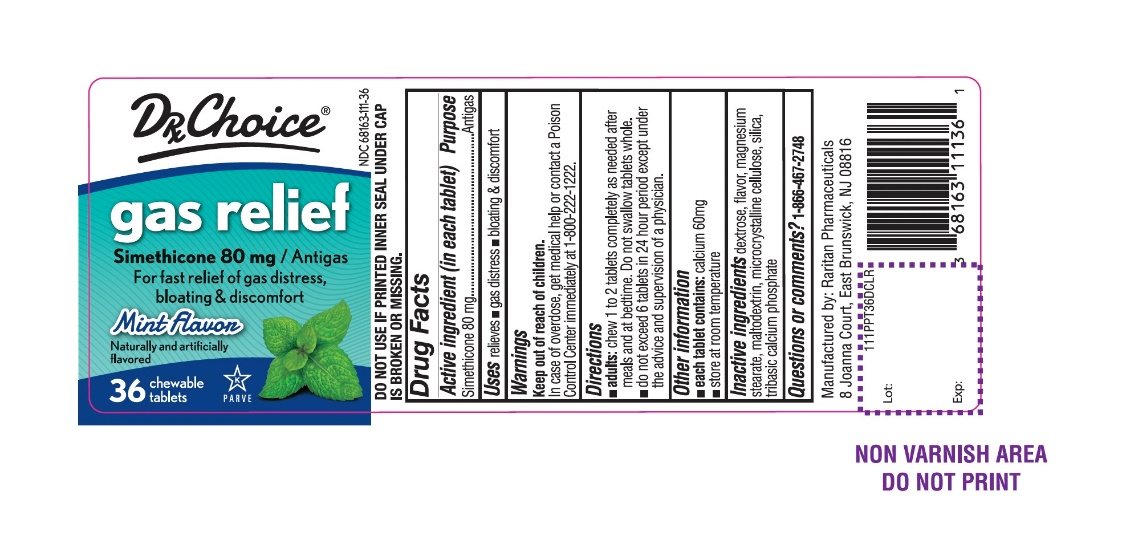 DRUG LABEL: Gas Relief

NDC: 68163-111 | Form: TABLET, CHEWABLE
Manufacturer: Raritan Pharmaceuticals Inc
Category: otc | Type: HUMAN OTC DRUG LABEL
Date: 20250926

ACTIVE INGREDIENTS: DIMETHICONE, UNSPECIFIED 80 mg/1 1
INACTIVE INGREDIENTS: DEXTROSE, UNSPECIFIED FORM; PEPPERMINT; MAGNESIUM STEARATE; MALTODEXTRIN; MICROCRYSTALLINE CELLULOSE; SILICON DIOXIDE; TRICALCIUM PHOSPHATE

DRxCHOICE Simethicone Gas Relief 36 Chewable Tablets

Active ingredient (in each tablet)

Simethicone 80 mg

Purpose

Antigas

Uses

Relieves:

- bloating
- pressure
- symptoms referred to as gas

Directions

- thoroughly chew 1 to 2 tablets as needed after meals and at bedtime
- do not exceed 4 tablets in 24 hours period except under the advice and supervision of a physician.

Other information

- store at room temperature 20-25ºC (68-77ºF)
- each tablets contains:calcium 60mg

Inactive ingredients

dextrose, peppermint flavor, magnesium stearate, maltodextrin, microcrystalline cellulose, silica, tribasic calcium phosphate

Principal Display Panel

NDC 68163-111-36

DRx CHOICE

Gas Relief

Anti Gas/Simethicone 80 mg

For fast relief of Bloating, Pressure & Gas Distress

Mint Flavor

Naturally and Artificially Flavored

36 CHEWABLE TABLETS

Manufactured by: Raritan Pharmaceuticals

8 Joanna Court, East Brunswick, NJ 08816